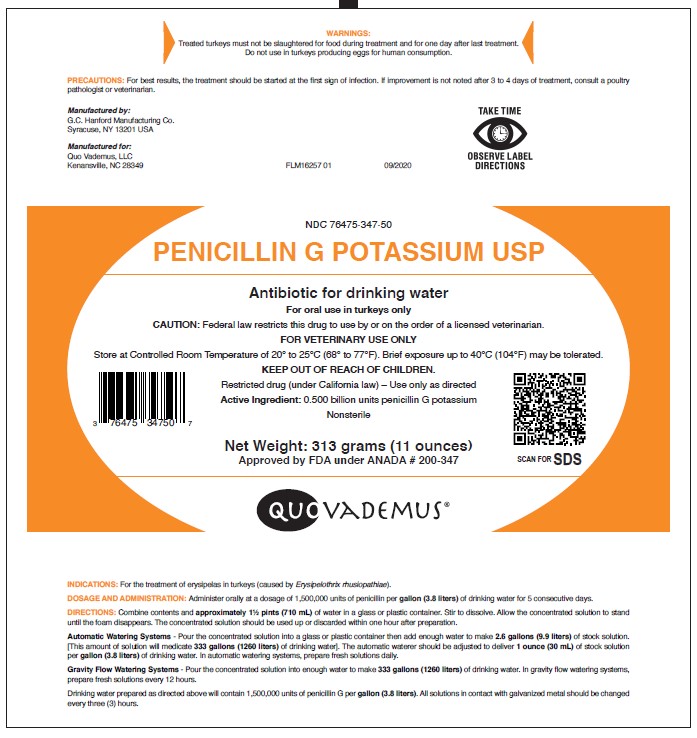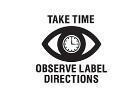 DRUG LABEL: Penicillin G Potassium
NDC: 76475-347 | Form: POWDER, FOR SOLUTION
Manufacturer: Quo Vademus LLC
Category: animal | Type: PRESCRIPTION ANIMAL DRUG LABEL
Date: 20230425

ACTIVE INGREDIENTS: PENICILLIN G POTASSIUM 500000000 [iU]/313 g

DESCRIPTION

NDC 76475-347-50

PENICILLIN G POTASSIUM USP

Antibiotic for drinking water

GENERAL PRECAUTIONS

For oral use in turkeys only

CAUTION: Federal law restricts this drug to use by or on the order of a licensed veterinarian.

FOR VETERINARY USE ONLY

Store at Controlled Room Temperature of 20° to 25°C (68° to 77°F). Brief exposure up to 40°C (104°F) may be tolerated.

KEEP OUT OF REACH OF CHILDREN

Restricted drug (under California law) - Use only as directed

Active Ingredient: 0.500 billion units penicillin G potassium

Nonsterile

Approved by FDA under ANADA # 200-347

QUO VADEMUS

INDICATIONS AND USAGE

INDICATIONS: For the treatment of erysipelas in turkeys (caused by Erysipelothrix rhusiopathiae).

DOSAGE AND ADMINISTRATION: Administer orally at a dosage of 1,500,000 units of penicillin per gallon (3.8 liters) of drinking water for 5 consecutive days.

DIRECTIONS: Combine contents and approximately 1 1/2 pints (710 mL) of water in a glass or plastic container. Stir to dissolve. Allow the concentrated solution to stand until the foam disappears. The concentrated solution should be used up or discarded within one hour after preparation.

Automatic Watering Systems - Pour the concentrated solution into a glass or plastic container then add enough water to make 2.6 gallons (9.9 liters) of stock solution. [This amount of solution will medicate 333 gallons (1260 liters) of drinking water]. The automatic waterer should be adjusted to deliver 1 ounce (30 mL) of stock solution per gallon (3.8 liters) of drinking water. In automatic watering systems, prepare fresh solutions daily.

Gravity Flow Watering Systems - Pour the concentrated solution into enough water to make 333 gallons (1260 liters) of drinking water. In gravity flow watering systems, prepare fresh solutions every 12 hours.

Drinking water prepared as directed above will contain 1,500,000 units of penicillin G per gallon (3.8 liters). All solutions in contact with galvanized metal should be changed every three (3) hours.

WARNINGS:

Treated turkeys must not be slaughtered for food during treatment and for one day after last treatment.

Do not use in turkeys producing eggs for human consumption.

PRECAUTIONS

PRECAUTIONS: For best results, the treatment should be started at the first sign of infection. If improvement is not noted after 3 to 4 days of treatment, consult a poultry pathologist or veterinarian.

Manufactured by:

G. C. Hanford Manufacturing Co.

Syracuse, NY 13201 USA

Manufactured for:

Quo Vademus, LLC

Kenansville, NC 28349

PRINCIPAL DISPLAY PANEL - 313 GRAM POUCH

NDC 76475-347-50

PENICILLIN G POTASSIUM USP

Antibiotic for drinking water

For oral use in turkeys only

CAUTION: Federal law restricts this drug to use by or on the order of a licensed veterinarian.

FOR VETERINARY USE ONLY

Store at Controlled Room Temperature of 20° to 25°C (68° to 77°F). Brief exposure up to 40°C (104°F) may be tolerated.

KEEP OUT OF REACH OF CHILDREN

Restricted drug (under California law) - Use only as directed

ACTIVE INGREDIENT: 0.500 billion units penicillin G potassium

Nonsterile

Net Weight: 313 grams (11 ounces)

Approved by FDA under ANADA # 200-347

QUO VADEMUS®